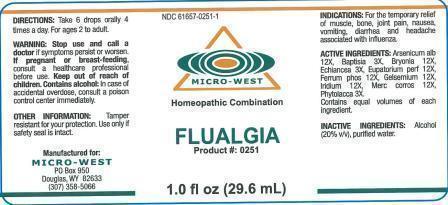 DRUG LABEL: Flualgia
NDC: 61657-0251 | Form: LIQUID
Manufacturer: White Manufacturing Inc. DBA Micro-West
Category: homeopathic | Type: HUMAN OTC DRUG LABEL
Date: 20140825

ACTIVE INGREDIENTS: GELSEMIUM SEMPERVIRENS ROOT 12 [hp_X]/30 mL; EUPATORIUM PERFOLIATUM FLOWERING TOP 12 [hp_X]/30 mL; FERROSOFERRIC PHOSPHATE 12 [hp_X]/30 mL; BRYONIA ALBA ROOT 12 [hp_X]/30 mL; MERCURIC CHLORIDE 12 [hp_X]/30 mL; ARSENIC TRIOXIDE 12 [hp_X]/30 mL; IRIDIUM 12 [hp_X]/30 mL; ECHINACEA, UNSPECIFIED 3 [hp_X]/30 mL; BAPTISIA TINCTORIA ROOT 3 [hp_X]/30 mL; PHYTOLACCA AMERICANA ROOT 3 [hp_X]/30 mL
INACTIVE INGREDIENTS: ALCOHOL

DRUG FACTS

ACTIVE INGREDIENTS

Arsenicum alb 12X

Baptisia 3X

Bryonia 12X

Echinacea 3X

Eupatorium perf 12X

Ferrum phos 12X

Gelsemium 12X

Iridium 12X

Merc corros 12X

Phytolacca 3X

PURPOSE

FOR THE TEMPORARY relief of muscle, bone, joint pain, nausea ,vomiting, diarrhea and headache associated with influenza

KEEP OUT OF REACH OF CHILDREN

INDICATIONS

INDICATIONS: For the temporary relief of muscle, bone, joint pain, nausea, vomiting, diarrhea and headache associated with influenza

WARNING

WARNINGS: STOP USE AND CALL A DOCTOR if symptoms persist or worsen. CONTAINS ALCOHOL: in case of accidental overdose, consult a poison control center immediately.

OTHER INFORMATION: Tamper resistant for your protection. Use only if safety seal is intact.

PREGNANCY OR BREAST-FEEDING

IF PREGNANT OR BREAST-FEEDING, consult a healthcare professional before use

DIRECTIONS

DIRECTIONS: Take 6 drops orally, 4 times a day. For ages 2 to adult

INACTIVE INGREDIENTS

Alcohol 20% v/v

Purified water

MANUFACTURE

MANUFACTURED FOR

MICRO-WEST

P.O. BOX 950

DOUGLAS, WY 82633

1-307-358-5066